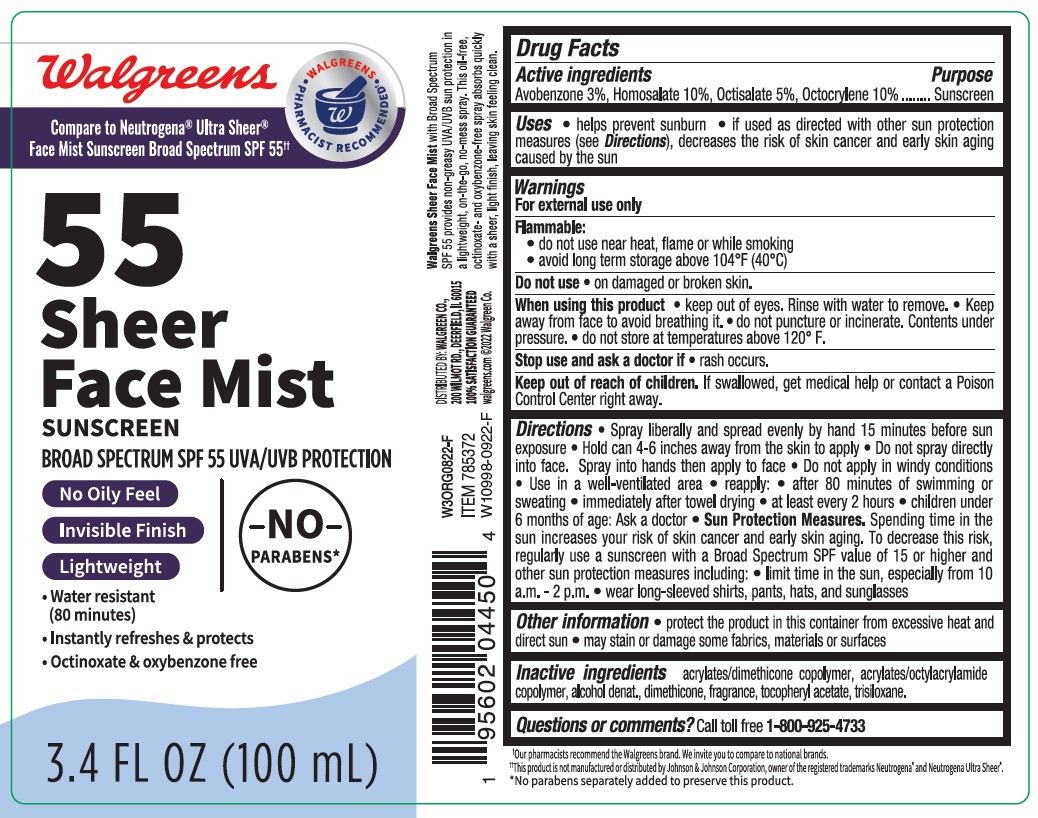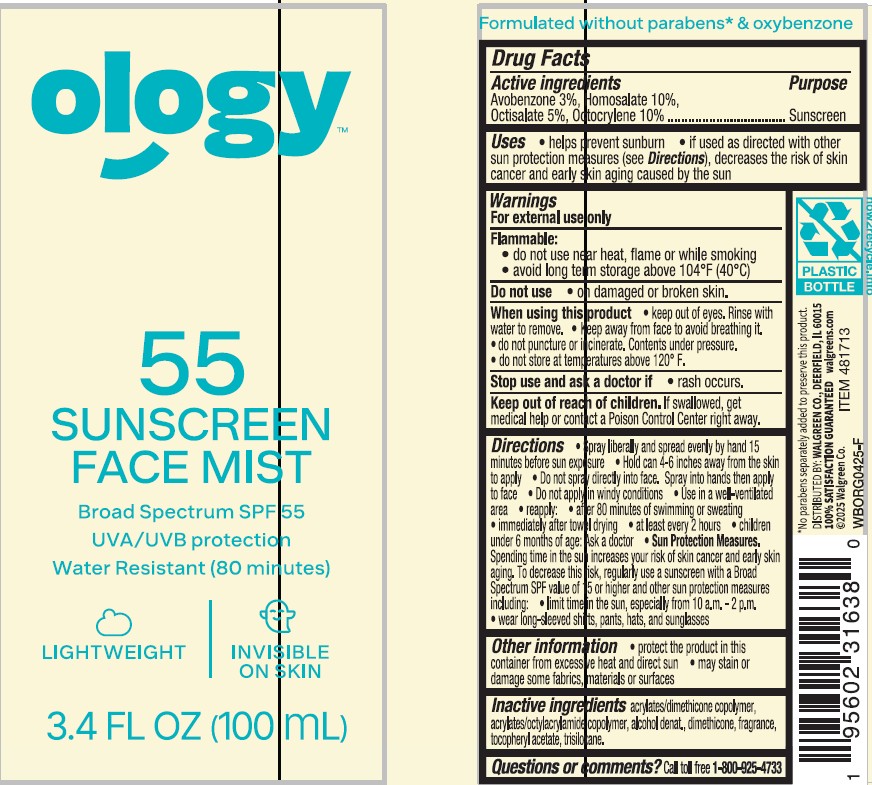 DRUG LABEL: Walgreens SPF 55 Sheer Face Mist Sunscreen
NDC: 0363-0053 | Form: SPRAY
Manufacturer: WALGREEN COMPANY
Category: otc | Type: HUMAN OTC DRUG LABEL
Date: 20250624

ACTIVE INGREDIENTS: AVOBENZONE 300 mg/10 mL; HOMOSALATE 1000 mg/10 mL; OCTISALATE 500 mg/10 mL; OCTOCRYLENE 1000 mg/10 mL
INACTIVE INGREDIENTS: DIMETHICONE; ALCOHOL; ACRYLATE/ISOBUTYL METHACRYLATE/N-TERT-OCTYLACRYLAMIDE COPOLYMER (75000 MW); TRISILOXANE; .ALPHA.-TOCOPHEROL ACETATE

Walgreens SPF 55 Sheer Face Mist Sunscreen

Active ingredients

Avobenzone 3.0%,

Homosalate 10.0%,

Octisalate 5.0%,

Octocrylene 10.0%

Purpose

Sunscreen

Uses

- helps prevent sunburn
- if used as directed with other sun protection measures (see Directions), decreases the risk of skin cancer and early skin aging caused by the sun

Warnings

For external use only

FLAMMABLE:

• do not use near heat, flame or while smoking
• avoid long term storage above 104°F (40°C)

Do not use

- on damaged or broken skin

When using this product

• keep out of eyes. Rinse with water to remove. • Keep away from face to avoid breathing it.

Stop use and ask doctor if

- rash occurs.

Keep out of reach of children.

If product is swallowed, get medical help or contact a Poison Control Center right away.

Directions

• Spray liberally and spread evenly by hand 15 minutes before sun exposure

• Hold can 4-6 inches away from skin to apply

• Do not spray into face. Spray into hand and apply to face.

- Do not apply in windy conditions

• Use in well-ventilated area
• reapply:
• after 80 minutes of swimming or sweating
• immediately after towel drying
• at least every 2 hours

- children under 6 months: Ask a doctor

- Sun Protection Measures. Spending time in the sun increases your risk of skin cancer and early skin aging. To decrease this risk, regularly use a sunscreen with a Broad Spectrum SPF value of 15 or higher and other sun protection measures including:

• limit time in the sun, especially from 10 a.m. - 2 p.m.
• wear long-sleeved shirts, pants, hats, and sunglasses

Other Information

• protect the product in this container from excessive heat and direct sun
• may stain or damage some fabrics, materials or surfaces

Inactive ingredients

acrylates/dimethicone copolymer, acrylates/octylacrylamide copolymer, alcohol denat.,dimethicone, fragrance, tocopherol acetate, trisiloxane.